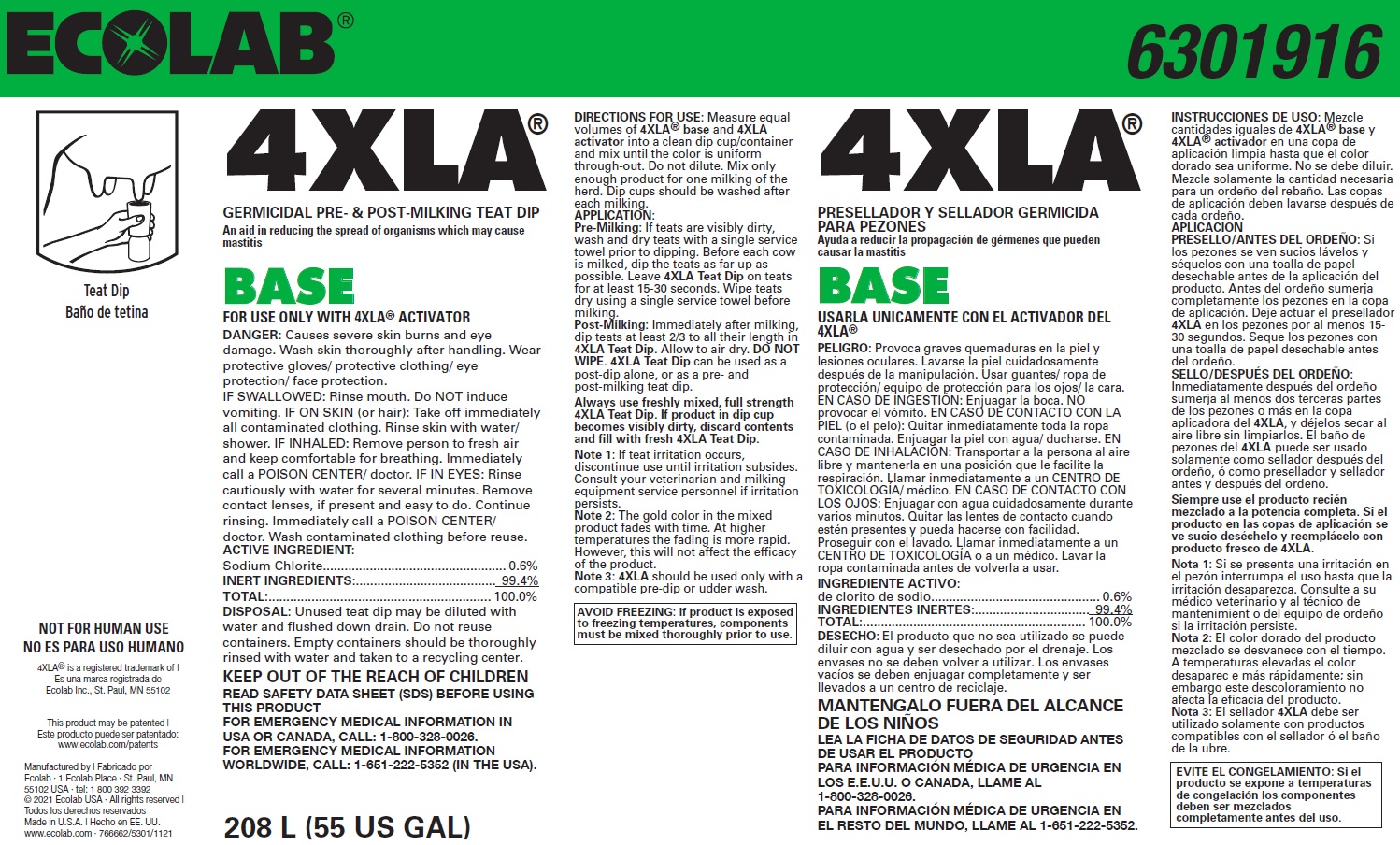 DRUG LABEL: 4XLA Base
NDC: 47593-607 | Form: SOLUTION
Manufacturer: Ecolab Inc.
Category: animal | Type: OTC ANIMAL DRUG LABEL
Date: 20251116

ACTIVE INGREDIENTS: SODIUM CHLORITE 6 mg/1 mL
INACTIVE INGREDIENTS: WATER

SAFE HANDLING WARNING

FOR USE ONLY WITH 4XLA® ACTIVATOR

DANGER: Causes severe skin burns and eye damage. Wash skin thoroughly after handling. Wear protective gloves/ protective clothing/ eye protection/ face protection.

DISPOSAL: Unused teat dip may be diluted with water and flushed down drain. Do not reuse containers. Empty containers should be thoroughly rinsed with water and taken to a recycling center.

KEEP OUT OF THE REACH OF CHILDREN

NOT FOR HUMAN USE

AVOID FREEZING: If product is exposed to freezing temperatures, components must be mixed thoroughly prior to use.

VETERINARY INDICATIONS

DIRECTIONS FOR USE: Measure equal volumes of 4XLA® base and 4XLA activator into a clean dip cup/container and mix until the color is uniform through-out. Do not dilute. Mix only enough product for one milking of the herd. Dip cups should be washed after each milking.

APPLICATION:

Pre-Milking: If teats are visibly dirty, wash and dry teats with a single service towel prior to dipping. Before each cow is milked, dip the teats as far up as possible. Leave 4XLA Teat Dip on teats for at least 15-30 seconds. Wipe teats dry using a single service towel before milking.

Post-Milking: Immediately after milking, dip teats at least 2/3 to all their length in 4XLA Teat Dip. Allow to air dry. DO NOT WIPE. 4XLA Teat Dip can be used as a post-dip alone, or as a pre- and post-milking teat dip.

Always use freshly mixed, full strength 4XLA Teat Dip. If product in dip cup becomes visibly dirty, discard contents and fill with fresh 4XLA Teat Dip.

Note 1: If teat irritation occurs, discontinue use until irritation subsides. Consult your veterinarian and milking equipment service personnel if irritation persists.

Note 2: The gold color in the mixed product fades with time. At higher temperatures the fading is more rapid. However, this will not affect the efficacy of the product.

Note 3: 4XLA should be used only with a compatible pre-dip or udder wash.

OTHER SAFETY INFORMATION

IF SWALLOWED: Rinse mouth. Do NOT induce vomiting. IF ON SKIN (or hair): Take off immediately all contaminated clothing. Rinse skin with water/ shower. IF INHALED: Remove person to fresh air and keep comfortable for breathing. Immediately call a POISON CENTER/ doctor. IF IN EYES: Rinse cautiously with water for several minutes. Remove contact lenses, if present and easy to do. Continue rinsing. Immediately call a POISON CENTER/ doctor. Wash contaminated clothing before reuse.

READ SAFETY DATA SHEET (SDS) BEFORE USING THIS PRODUCT

FOR EMERGENCY MEDICAL INFORMATION IN USA OR CANADA, CALL: 1-800-328-0026.

FOR EMERGENCY MEDICAL INFORMATION WORLDWIDE, CALL: 1-651-222-5352 (IN THE USA).

Principal display panel and representative container

4XLA 6302478

GERMICIDAL PRE- & POST-MILKING TEAT DIP

An aid in reducing the spread of organisms which may cause mastitis

BASE

ACTIVE INGREDIENT:

Sodium Chlorite................................................... 0.6%

INERT INGREDIENTS:....................................... 99.4%

TOTAL:.............................................................. 100.0%

208 L (55 US GAL)

Manufactured by | Fabricado por Ecolab · 1 Ecolab Place · St. Paul, MN 55102 USA · tel: 1 800 392 3392

© 2021 Ecolab USA · All rights reserved | Todos los derechos reservados

Made in U.S.A. | Hecho en EE. UU. www.ecolab.com · 766662/5301/1121